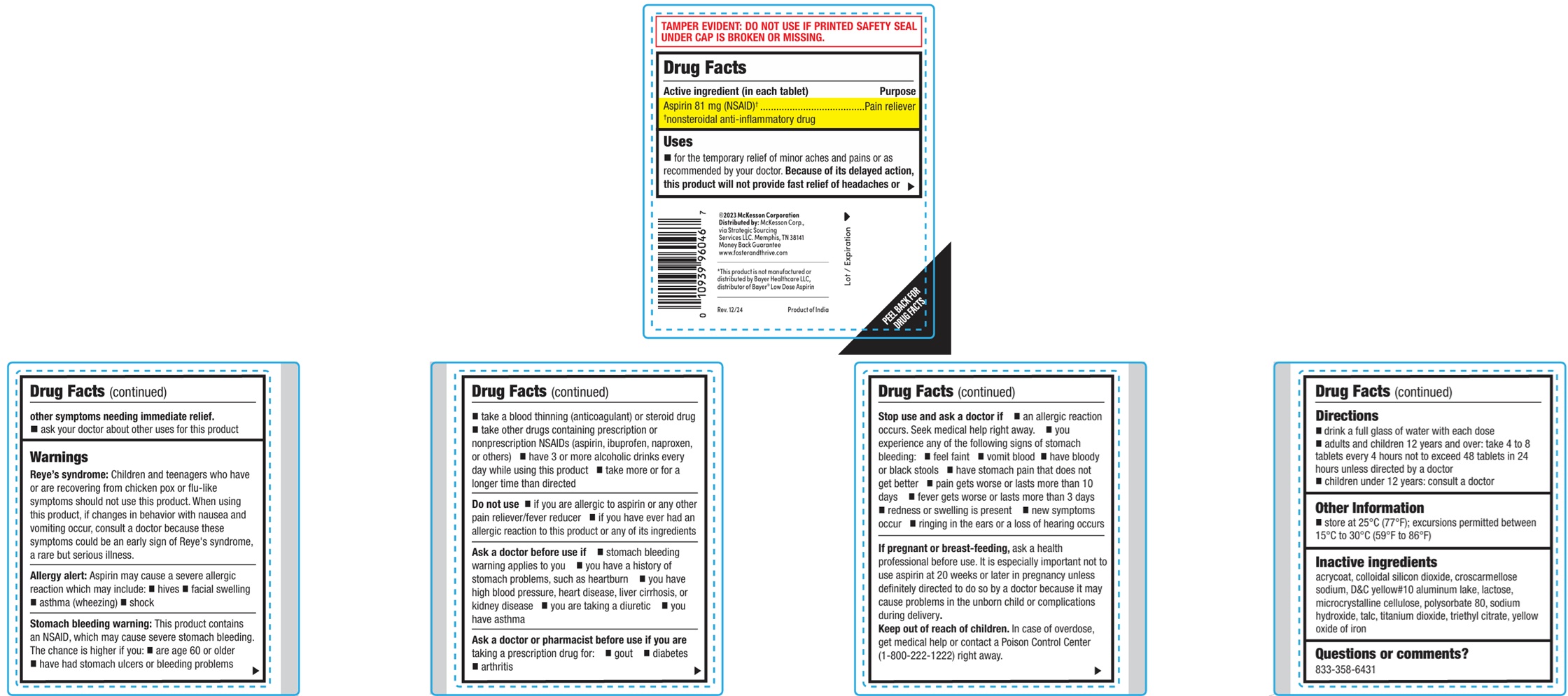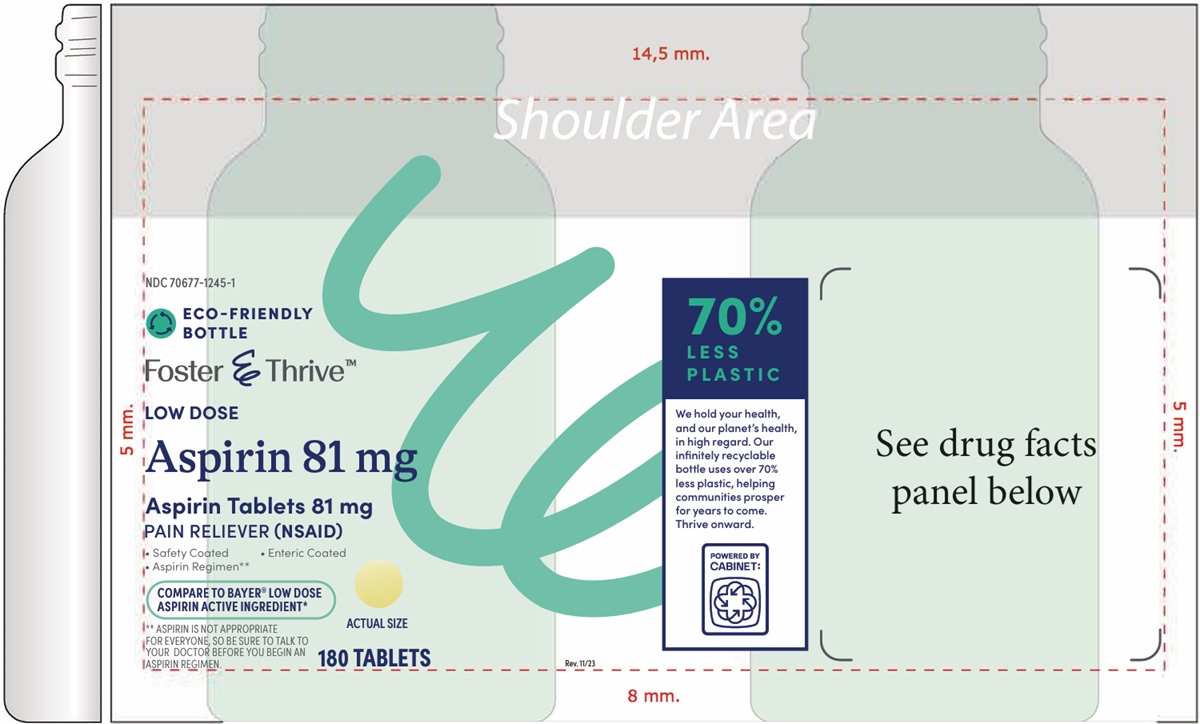 DRUG LABEL: ASPIRIN
NDC: 70677-1245 | Form: TABLET
Manufacturer: Strategic Sourcing Services LLC
Category: otc | Type: HUMAN OTC DRUG LABEL
Date: 20260129

ACTIVE INGREDIENTS: ASPIRIN 81 mg/1 1
INACTIVE INGREDIENTS: METHACRYLIC ACID - METHYL METHACRYLATE COPOLYMER (1:1); SILICON DIOXIDE; CROSCARMELLOSE SODIUM; D&C YELLOW NO. 10 ALUMINUM LAKE; LACTOSE, UNSPECIFIED FORM; MICROCRYSTALLINE CELLULOSE; POLYSORBATE 80; SODIUM HYDROXIDE; TALC; TITANIUM DIOXIDE; TRIETHYL CITRATE; FERRIC OXIDE YELLOW

LOW DOSE ASPIRIN